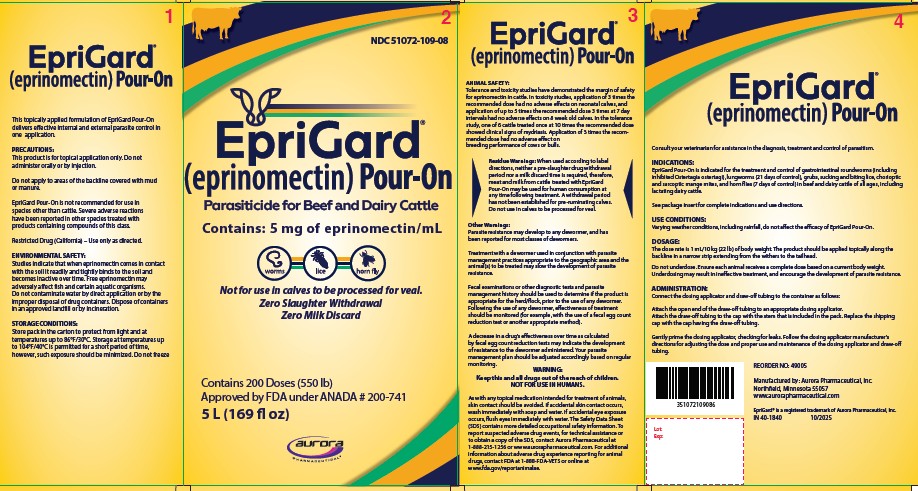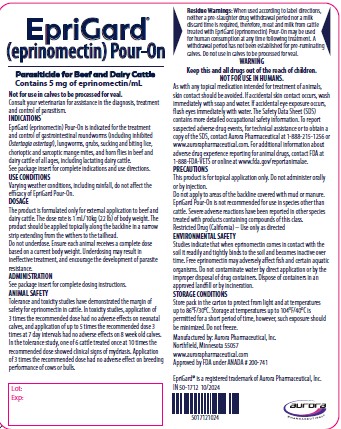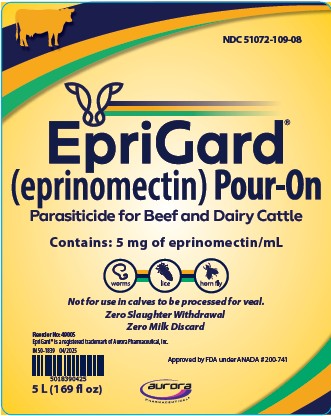 DRUG LABEL: EpriGard
NDC: 51072-109 | Form: SOLUTION
Manufacturer: Aurora Pharmaceutical, Inc.
Category: animal | Type: OTC ANIMAL DRUG LABEL
Date: 20260216

ACTIVE INGREDIENTS: eprinomectin 5 mg/1 mL

EpriGard®
(eprinomectin) Pour-On

Parasiticide for Beef and Dairy Cattle

Contains 5 mg eprinomectin/mL

Not for use in calves to be processed for veal.

INTRODUCTION

EpriGard Pour-On delivers effective internal and external parasite control in one application. EpriGard Pour-On contains eprinomectin, a unique avermectin. Its broad-spectrum efficacy in a weatherproof formulation, margin of safety, zero slaughter withdrawal and zero milk discard, make it a convenient product for parasite control in beef and dairy cattle, including lactating dairy cattle.

MODE OF ACTION

Eprinomectin is a member of the macrocyclic lactone class of endectocides which have a unique mode of action. Compounds of the class bind selectively and with high affinity to glutamate-gated chloride ion channels which occur in invertebrate nerve and muscle cells.

This leads to an increase in the permeability of the cell membrane to chloride ions with hyperpolarization of the nerve or muscle cell, resulting in paralysis and death of the parasite. Compounds of this class may also interact with other ligand-gated chloride channels, such as those gated by the neurotransmitter gamma-aminobutyric acid (GABA).

The margin of safety for compounds of this class is attributable to the fact that mammals do not have glutamate-gated chloride channels, the macrocyclic lactones have a low affinity for other mammalian ligand-gated chloride channels and they do not readily cross the blood-brain barrier.

INDICATIONS

EpriGard (eprinomectin) Pour-On is indicated for the treatment and control of gastrointestinal roundworms (including inhibited Ostertagia ostertagi), lungworms, grubs, sucking and biting lice, chorioptic and sarcoptic mange mites, and horn flies in beef and dairy cattle of all ages, including lactating dairy cattle.

Applied at the recommended dose volume of 1 mL/10 kg (22 lb) body weight, to achieve a dose level of 500 mcg eprinomectin/kg body weight, EpriGard Pour-On is indicated for the effective treatment and control of the following parasites.

Gastrointestinal Roundworms
Haemonchus placei | (adults and L4)
Ostertagia ostertagi (including inhibited L4) | (adults and L4)
Trichostrongylus axei | (adults and L4)
Trichostrongylus colubriformis | (adults and L4)
Trichostrongylus longispicularis | (adults only)
Cooperia oncophora | (adults and L4)
Cooperia punctata | (adults and L4)
Cooperia surnabada | (adults and L4)
Nematodirus helvetianus | (adults and L4)
Oesophagostomum radiatum | (adults and L4)
Bunostomum phlebotomum | (adults and L4)
Strongyloides papillosus | (adults only)
Trichuris spp. | (adults only)
Lungworms
Dictyocaulus viviparus | (adults and L4)
Cattle Grubs (all parasitic stages)
Hypoderma lineatum, Hypoderma bovis
Lice
Damalinia bovis, Linognathus vituli, Haematopinus
eurysternus, Solenopotes capillatus
Mange Mites
Chorioptes bovis, Sarcoptes scabiei
Horn Flies
Haematobia irritans

Persistent Activity

EpriGard (eprinomectin) Pour-On for Beef and Dairy Cattle has been proved to effectively control infections and to protect cattle from re-infection with Dictyocaulus viviparus for 21 days after treatment and Haematobia irritans for 7 days after treatment.

Use Conditions

Varying weather conditions, including rainfall, do not affect the efficacy of EpriGard Pour-On.

Management Considerations for Treatment of External Parasites

For best results EpriGard Pour-On should be applied to all cattle in the herd. Cattle introduced to the herd later should be treated prior to introduction. Consult your veterinarian or an entomologist for the most effective timing of applications for the control of external parasites.

Chorioptic Mange: In clinical studies evaluating the efficacy of eprinomectin Pour-On against chorioptic mange mites, mites were not recovered from skin scrapings taken 8 weeks after treatment; however, chronic skin lesions were still present on some animals.

Horn flies: For optimal control of horn flies, as EpriGard Pour-On provides 7 days of persistent activity against horn flies, the product should be used as part of an integrated control program utilizing other control methods to provide extended control.

DOSAGE

The product is formulated only for external application to beef and dairy cattle. The dose rate is 1 mL/10 kg (22 lb) of body weight. The product should be applied topically along the backline in a narrow strip extending from the withers to the tailhead.

Do not underdose. Ensure each animal receives a complete dose based on a current body weight. Underdosing may result in ineffective treatment, and encourage the development of parasite resistance.

ADMINISTRATION

Metering Cup with Measure-Squeeze-Pour System

250 mL (8.5 fl oz) Container with 25 mL Metering Cup

This pack contains 1 Metering Cup and 1 dip tube

1. Insert the dip tube into base of the Metering Cup. Leave the "slotted end" of the dip tube exposed in the bottom of the container.

2. Unscrew shipping cap from container top.

3. Screw the Metering Cup onto container top.

4. Measure: To select the correct dose rate, rotate the adjuster cap (top) in either direction to position the dose indicator to the weight of the animal you want to treat. When body weight is between markings, use the higher setting.

5. Squeeze the container gently to fill the Metering Cup to the required dose. Release your grip and any excess will return to the container.

6. Pour: Apply the full dose by tipping and pouring along the backline of the animal until the Metering Cup is empty.

7. Storage: The Metering Cup should not remain attached to the container when not in use. Detach the Metering Cup after each use and replace the shipping cap to close the container top.

Backpack (1 L/33.8 fl oz, 2.5 L/84.5 fl oz, and 5 L/169 fl oz Packs) and 10 L/338 fl oz Pack

Connect the dosing applicator and draw-off tubing to the backpack as follows:

Attach the open end of the draw-off tubing to an appropriate dosing applicator. Attach draw-off tubing to the cap with the stem that is included in the pack. Replace the shipping cap with the cap having the draw-off tubing.

Gently prime the dosing applicator, checking for leaks. Follow the dosing applicator manufacturer's directions for adjusting the dose and proper use and maintenance of the dosing applicator and draw-off tubing.

ANIMAL SAFETY

Tolerance and toxicity studies have demonstrated the margin of safety for eprinomectin in cattle. In toxicity studies, application of 3 times the recommended dose had no adverse effects on neonatal calves, and application of up to 5 times the recommended dose 3 times at 7 day intervals had no adverse effects on 8 week old calves. In the tolerance study, one of 6 cattle treated once at 10 times the recommended dose showed clinical signs of mydriasis. Application of 3 times the recommended dose had no adverse effect on breeding performance of cows or bulls.

RESIDUE WARNING

Residue Warnings: When used according to label directions, neither a pre-slaughter drug withdrawal period nor a milk discard time is required, therefore, meat and milk from cattle treated with EpriGard (eprinomectin) Pour-On may be used for human consumption at any time following treatment. A withdrawal period has not been established for pre-ruminating calves. Do not use in calves to be processed for veal.

WARNING:

Keep this and all drugs out of the reach of children.

NOT FOR USE IN HUMANS.

As with any topical medication intended for treatment of animals, skin contact should be avoided. If accidental skin contact occurs, wash immediately with soap and water. If accidental eye exposure occurs, flush eyes immediately with water. The Safety Data Sheet (SDS) contains more detailed occupational safety information.

To report suspected adverse drug events, for technical assistance, or to obtain a copy of the SDS, contact Aurora Pharmaceutical at 1-888-215-1256 or www.aurorapharmaceutical.com. For additional information about adverse drug experience reporting for animal drugs, contact FDA at 1-888-FDA-VETS, or online at www.fda.gov/reportanimalae.

PRECAUTIONS

This product is for topical application only. Do not administer orally or by injection.

Do not apply to areas of the backline covered with mud or manure.

EpriGard Pour-On is not recommended for use in species other than cattle. Severe adverse reactions have been reported in other species treated with products containing compounds of this class.

Restricted Drug (California) - Use only as directed.

When to Treat Cattle with Grubs

EpriGard Pour-On is effective against all stages of cattle grubs. However, proper timing of treatment is important. For the most effective results, cattle should be treated as soon as possible after the end of the heel fly (warble fly) season. While this is not peculiar to eprinomectin, destruction of Hypoderma larvae (cattle grubs) at the period when these grubs are in vital areas may cause undesirable host-parasite reactions. Killing Hypoderma lineatum when it is in the esophageal tissues may cause bloat; killing H. bovis when it is in the vertebral canal may cause staggering or paralysis. Cattle should be treated either before or after these stages of grub development.

Cattle treated with EpriGard Pour-On at the end of the fly season may be re-treated with EpriGard Pour-On during the winter without danger of grub-related reactions. For further information and advice on a planned parasite control program, consult your veterinarian.

OTHER WARNINGS

Parasite resistance may develop to any dewormer, and has been reported for most classes of dewormers.

Treatment with a dewormer used in conjunction with parasite management practices appropriate to the geographic area and the animal(s) to be treated may slow the development of parasite resistance.

Fecal examinations or other diagnostic tests and parasite management history should be used to determine if the product is appropriate for the herd/flock, prior to the use of any dewormer. Following the use of any dewormer, effectiveness of treatment should be monitored (for example, with the use of a fecal egg count reduction test or another appropriate method).

A decrease in a drug’s effectiveness over time as calculated by fecal egg count reduction tests may indicate the development of resistance to the dewormer administered. Your parasite management plan should be adjusted accordingly based on regular monitoring.

Environmental Safety

Studies indicate that when eprinomectin comes in contact with soil, it readily and tightly binds to the soil and becomes inactive over time. Free eprinomectin may adversely affect fish and certain aquatic organisms. Do not permit cattle to enter lakes, streams or ponds for at least 6 hours after treatment. Do not contaminate water by direct application or by the improper disposal of drug containers. Dispose of containers in an approved landfill or by incineration.

As with other avermectins, eprinomectin is excreted in the dung of treated animals and can inhibit the reproduction and growth of pest and beneficial insects that use dung as a source of food and for reproduction. The magnitude and duration of such effects are species and life-cycle specific. When used according to label directions, the product is not expected to have an adverse impact on populations of dung-dependent insects.

ADVERSE REACTIONS

No adverse reactions were observed during clinical trials.

STORAGE CONDITIONS

Store bottle or pack in the carton to protect from light and at temperatures up to 86°F/30°C. Storage at temperatures up to 104°F/40°C is permitted for a short period of time, however, such exposure should be minimized. Do not freeze.

For the 250 mL/8.5 fl oz bottle with a measure-squeeze-pour system, the Metering Cup should not remain attached to the container when not in use. Detach the Metering Cup after each use and replace the shipping cap to close the container top.

HOW SUPPLIED

EpriGard (eprinomectin) Pour-On for Beef and Dairy Cattle is available in a 250 mL/8.5 fl oz bottle with a measure-squeeze-pour system, or in a 1L/33.8 fl oz, 2.5 L/84.5 fl oz, or 5 L/169 fl oz backpack, or 10 L/338 fl oz pack, intended for use with appropriate automatic dosing equipment.

Approved by FDA under ANADA # 200-741

Manufactured by: Aurora Pharmaceutical, Inc.

Northfield, Minnesota 55057

Principal Display Panel - 5000 mL Bottle Carton

EpriGard®

(eprinomectin) Pour-On

Parasiticide for Beef and Dairy Cattle
Contains 5 mg eprinomectin/mL

Not for use in calves to be processed for veal.
Zero Slaughter Withdrawal
Zero Milk Discard

Contains 200 Doses (550 lb)

Approved by FDA under ANADA # 200-741

5000 mL (169 fl oz)

EpriGard® is a registered trademark of Aurora Pharmaceutical, Inc.

Reorder# 49005

IN 40-1840

rev 10/2025

Principal Display Panel – 5000 mL Container Label

EpriGard®

(eprinomectin) Pour-On

Parasiticide for Beef and Dairy Cattle
Contains 5 mg eprinomectin/mL

Not for use in calves to be processed for veal.
Zero Slaughter Withdrawal
Zero Milk Discard

Approved by FDA under ANADA # 200-741

5000 mL (169 fl oz)

EpriGard® is a registered trademark of Aurora Pharmaceutical, Inc.

Reorder# 49005

IN 50-1839

rev 04/2025

IN 50-1712

rev 10-2024